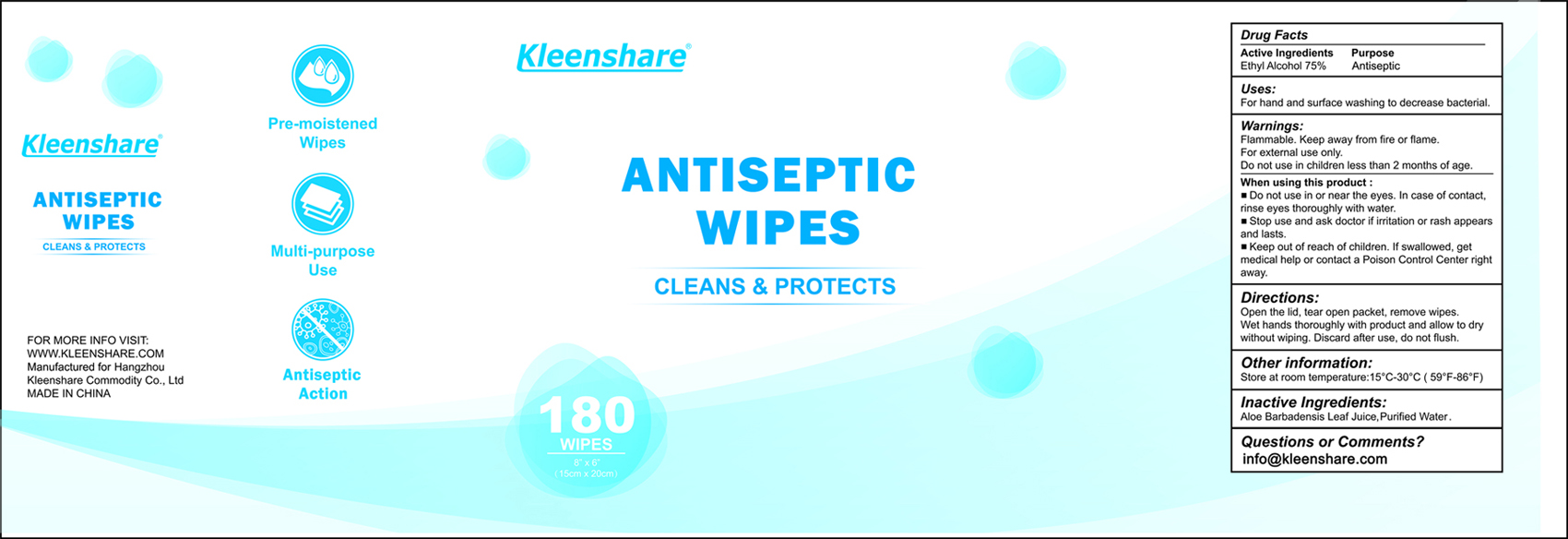 DRUG LABEL: Antibacterial/Antiseptic/Disinfecting Wipes
NDC: 80980-001 | Form: CLOTH
Manufacturer: Hangzhou Kleenshare Commodity Co., Ltd
Category: otc | Type: HUMAN OTC DRUG LABEL
Date: 20201101

ACTIVE INGREDIENTS: ALCOHOL 75 mL/100 g
INACTIVE INGREDIENTS: ALOE VERA LEAF; WATER

Antibacterial/Antiseptic/Disinfecting Wipes

Active Ingredients

Ethyl Alcohol 75% Antiseptic

Purpose

Antiseptic

Uses

For hand and surface washing to decrease bacterial.

Warnings

Flammable. Keep away from fire or flame.

For external use only

Do not use in children less than 2 months of age

When using this product

- Do not use in or near they eyes. In case of contact, rinse eyes thoroughly with water

Stop use and ask a doctor if irritation or rash appears and lasts.

Keep out of reach of children. If swallowed, get medical help or contact a Poison Control Center right away.

Directions

Open the lid, tear open packet, remove wipes

Wet hands thoroughly with product and allow to dry without wiping. Discard after use, do not flush..

Other information

Store at room temperature: 15C-30C (59F-86F)

Inactive Ingredients

Aloe Barbadensis Leaf Joice, Purified Water

Questions or Comments?

info@kleenshare.com

PACKAGE LABEL

80980-001-01 180 PCS

Kleenshare

Antiseptic

Wipes

Cleans & Protects

180

Wipes

8" x 6"

(15cm x 20cm)